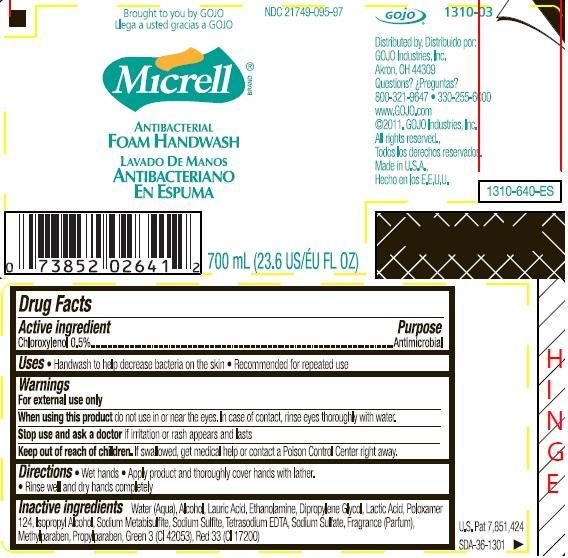 DRUG LABEL: MICRELL Antibacterial Foam Handwash
NDC: 21749-095 | Form: LIQUID
Manufacturer: GOJO Industries, Inc.
Category: otc | Type: HUMAN OTC DRUG LABEL
Date: 20260112

ACTIVE INGREDIENTS: CHLOROXYLENOL 0.005 mg/1 mL
INACTIVE INGREDIENTS: WATER; ALCOHOL; LAURIC ACID; MONOETHANOLAMINE; DIPROPYLENE GLYCOL; LACTIC ACID; POLOXAMER 124; ISOPROPYL ALCOHOL; SODIUM METABISULFITE; SODIUM SULFITE; EDETATE SODIUM; SODIUM SULFATE; METHYLPARABEN; PROPYLPARABEN; FD&C GREEN NO. 3; D&C RED NO. 33

MICRELL Antibacterial Foam Handwash

Active ingredient

Chloroxylenol 0.5%

Purpose

Antimicrobial

Use

- Handwash to help decrease bacteria on the skin
- Recommended for repeated use

Warnings

For external use only

WHEN USING

When using this productdo not use in or near the eyes. In case of contact, rinse eyes thoroughly with water.

Stop use and ask a doctor ifirritation or rash appears and lasts.

Keep out of reach of children.If swallowed, get medical help or contact a Poison Control Center right away.

Directions

- Wet hands.
- Apply product and thoroughly cover hands with lather.
- Rinse well and dry hands completely.

Inactive ingredients

Water (Aqua), Alcohol, Lauric Acid, Ethanolamine, Dipropylene Glycol, Lactic Acid, Poloxamer 124, Isopropyl Alcohol, Sodium Metabisulfite, Sodium Sulfite, Tetrasodium EDTA, Sodium Sulfate, Fragrance (Parfum), Methylparaben, Propylparaben, Green 3 (CI 42053), Red 33 (CI 17200)